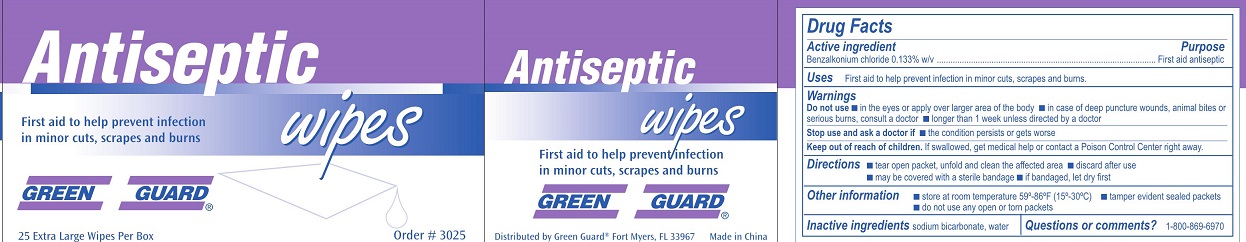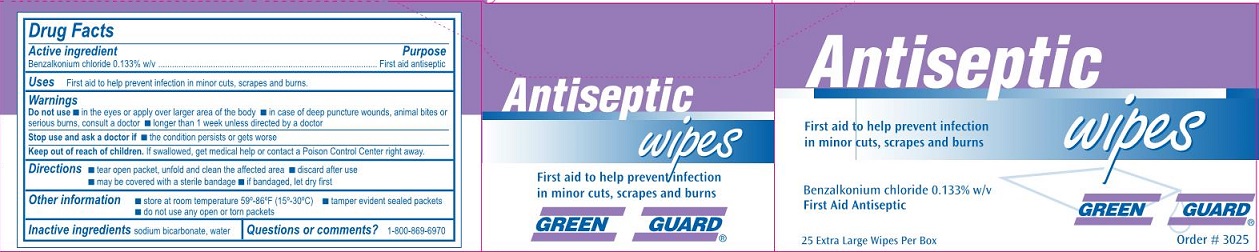 DRUG LABEL: Green Guard Antiseptic Wipes
NDC: 47682-045 | Form: SWAB
Manufacturer: Uniforst First Aid Corporation
Category: otc | Type: HUMAN OTC DRUG LABEL
Date: 20250908

ACTIVE INGREDIENTS: BENZALKONIUM CHLORIDE 1.3 mg/1 mL
INACTIVE INGREDIENTS: SODIUM BICARBONATE; WATER

Green Guard Antiseptic Wipes

Drug Facts

Active ingredient

Benzalkonium chloride 0.133% w/v

Purpose

First aid antiseptic

Uses

First aid to help prevent infection in minor cuts, scrapes and burns.

Warnings

Do not use

- in the eyes or applyover large area of the body
- in case of deep puncture wounds, animal bites or serious burns, consult a doctor
- longer than 1 week unless directed by a doctor

Stop use and ask a doctor if

- the condition persists or gets worse

Keep out of reach of children.

If swallowed, get medical help or contact a Poison Control Center right away.

Directions

- tear open packet, unfold and clean the affected area
- discard after use
- may be covered with a sterile bandage
- if bandaged, let dry first

Other information

- store at room temperature 59°-86°F (15°-30°C)
- tamper evident sealed packets
- do not use any open or toen packets

Inactive ingredients

sodium bicarbonate, water

Questions or comments?

1-800-869-6970

Green Guard Antiseptic Wipes Label

Antiseptic wipes

First aid to help prevent infection

in minor cuts, scrapes and burns

Benzalkonium chlorise 0.133% w/v

First Aid Antiseptic

Green Guard®

25 Extra Large Wipes Per Box

Order # 3025

Green Guard Antiseptic Wipes Exra Large Label

Antiseptic wipes

First aid to help prevent infection

in minor cuts, scrapes and burns

Green Guard®

25 Extra Large Wioes Per Box

Order # 3025